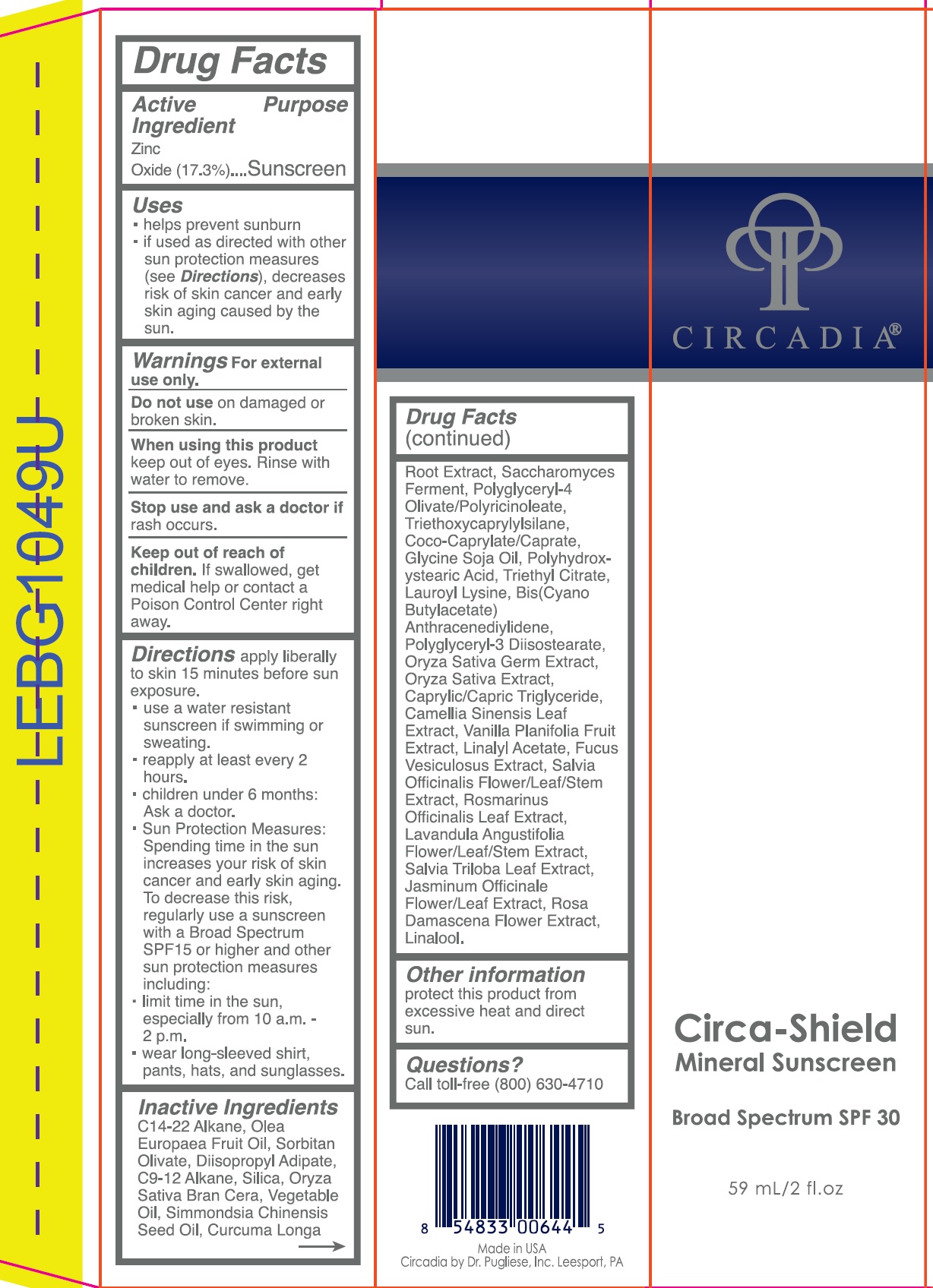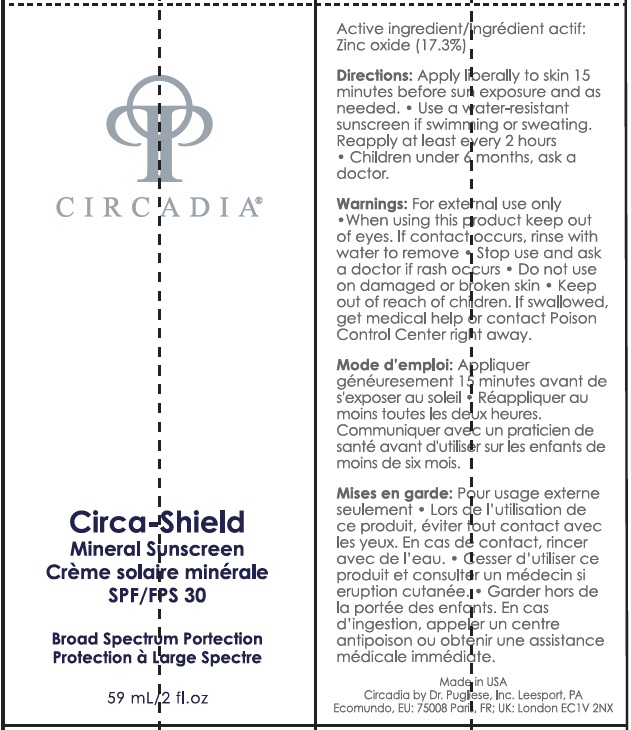 DRUG LABEL: Circadia Circa-Shield Mineral Sunscreen SPF 30
NDC: 76458-401 | Form: CREAM
Manufacturer: Circadia by Dr Pugliese, Inc.
Category: otc | Type: HUMAN OTC DRUG LABEL
Date: 20231222

ACTIVE INGREDIENTS: ZINC OXIDE 173 mg/1 mL
INACTIVE INGREDIENTS: OLIVE OIL; SORBITAN OLIVATE; DIISOPROPYL ADIPATE; C9-12 ALKANE; SILICON DIOXIDE; JOJOBA OIL; TURMERIC; POLYGLYCERYL-4 OLIVATE/POLYRICINOLEATE; TRIETHOXYCAPRYLYLSILANE; COCO-CAPRYLATE; TRIETHYL CITRATE; LAUROYL LYSINE; POLYGLYCERYL-3 DIISOSTEARATE; MEDIUM-CHAIN TRIGLYCERIDES; GREEN TEA LEAF; VANILLA BEAN; ROSEMARY; LAVANDULA ANGUSTIFOLIA SUBSP. ANGUSTIFOLIA FLOWER; THREE-LOBE SAGE; JASMINUM OFFICINALE FLOWER; ROSA X DAMASCENA FLOWER; LINALOOL, (+/-)-

Circadia Circa-Shield Mineral Sunscreen SPF 30

Active Ingredient

Zinc Oxide (17.3%)

Purpose

Sunscreen

Uses

- helps prevent sunburn.
- If used as directed with other sun protection measures (see Directions), decreases the risk of skin cancer and early skin aging caused by the sun.

Warnings

For external use only.

Do not use

on damaged or broken skin.

When using this product

keep out of eyes. Rinse with water to remove.

Stop use and ask a doctor if

rash occurs

Keep out of reach of children.

If swallowed, get medical help or contact a Poison Control Center right away.

Directions

apply liberally to skin 15 minutes before sun exposure.

- use a water resistant sunscreen if swimming or sweating.
- reapply at least every 2 hours.
- children under 6 months: Ask a doctor.
- Sun Protection Measures: Spending time in the sun increases your risk of skin cancer and early skin aging. To decrease this risk, regularly use a sunscreen with Broad Spectrum SPF or higher and other sun protection measures including:
- limit time in the sun, especially from 10 a.m. - 2 p.m.
- wear long-sleeved shirt, pants, hats and sunglasses.

Inactive Ingredients

C14-22 Alkane, Olea Europaea fruit Oil, Sorbitan Olivate, Diisopropyl Adipate, C9-12 Alkane, Silica, Oryza Sativa Bran Cera, Vegetable Oil, Simmondsia Chinensis Seed Oil, Curcuma Longa Root Extract, Saccharomyces Ferment, Polyglyceryl-4 Olivate/Polyricinoleate, Triethoxycaprylylsilane, Coco-Caprylate, Glycine Soja Oil, Polyhydroxystearic Acid, Triethyl Citrate, Lauroyl Lysine, Bis(Cyano Butylacetate) Antharacenediylidene, Polyglyceryl-3 Diisostearate, Oryza Sativa Germ Extract Oryza Sativa Extract, Caprylic /Capric Triglyceride, Camellia Sinensis Leaf Extract, Vanila Planifolia Fruit Extract, Salvia Officinalis Flower/Leaf/Stem Extract, Rosmarinus Officinalis Leaf Extract, Lavandula Angustifolia Flower/Leaf/Stem Extract, Salvia Triloba Leaf Extract, Jasminum Officinale Flower/Leaf Extract, Rosa Damascena Flower Extract, Linalool.

Other information

protect this product from excessive heat and direct sun.

Questions?

Call toll-free (800) 630-4710